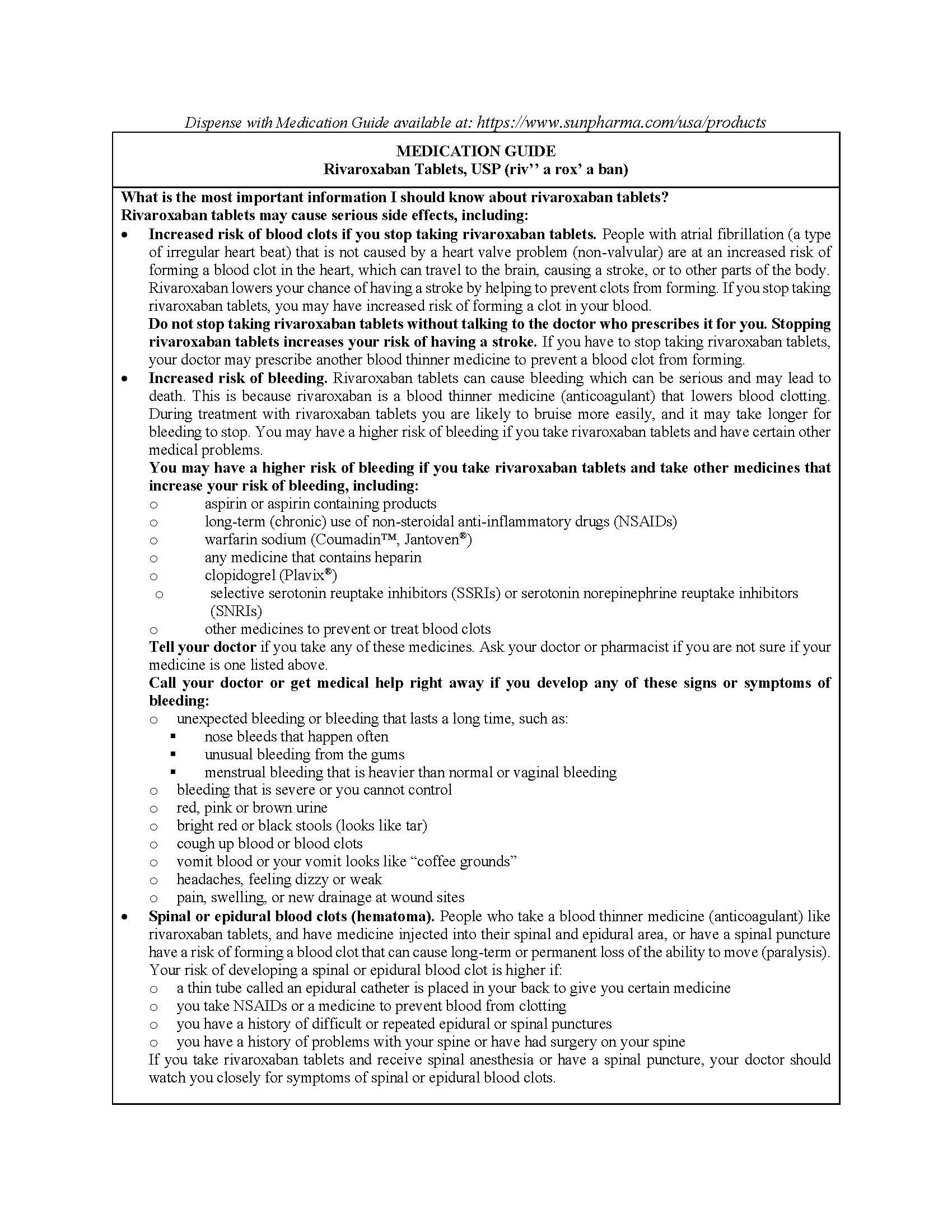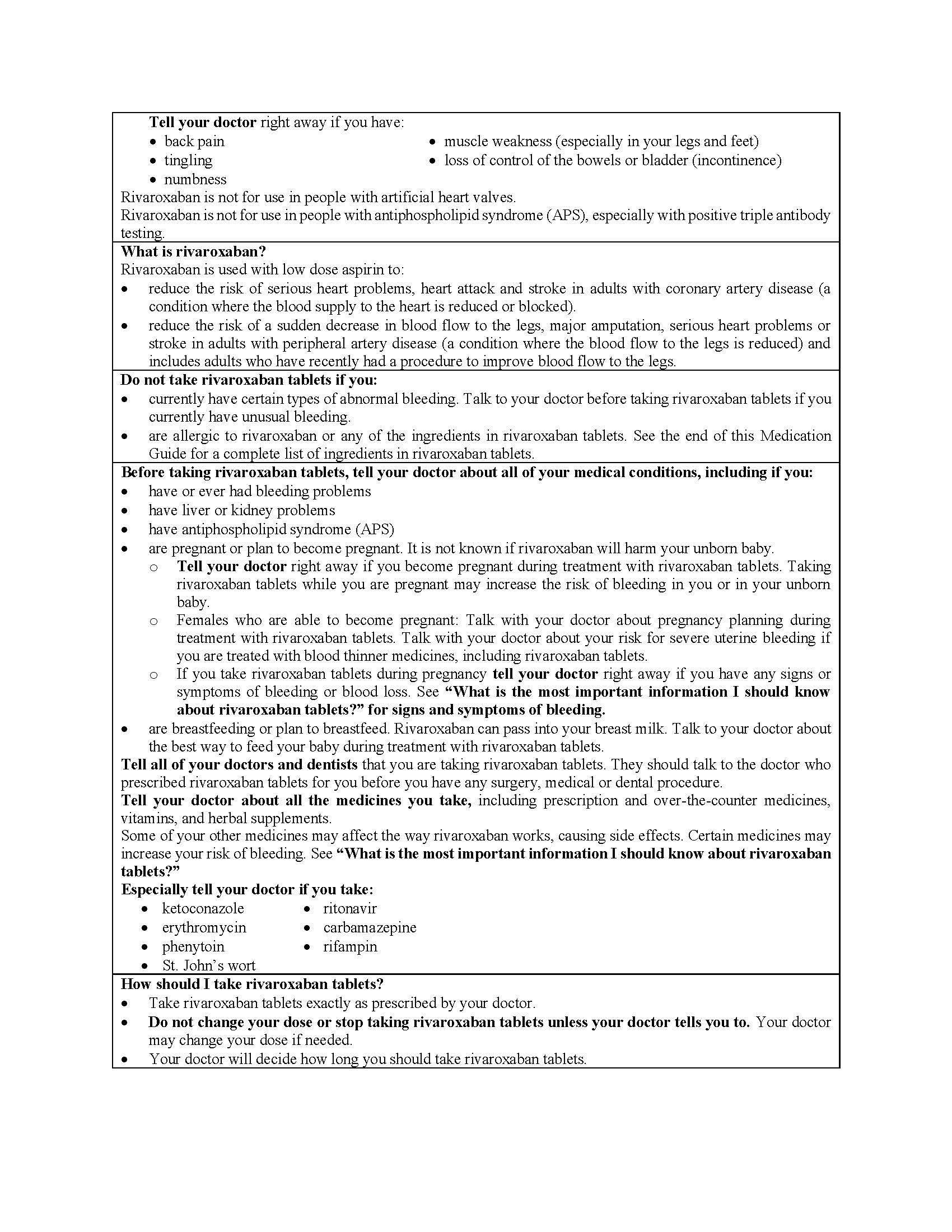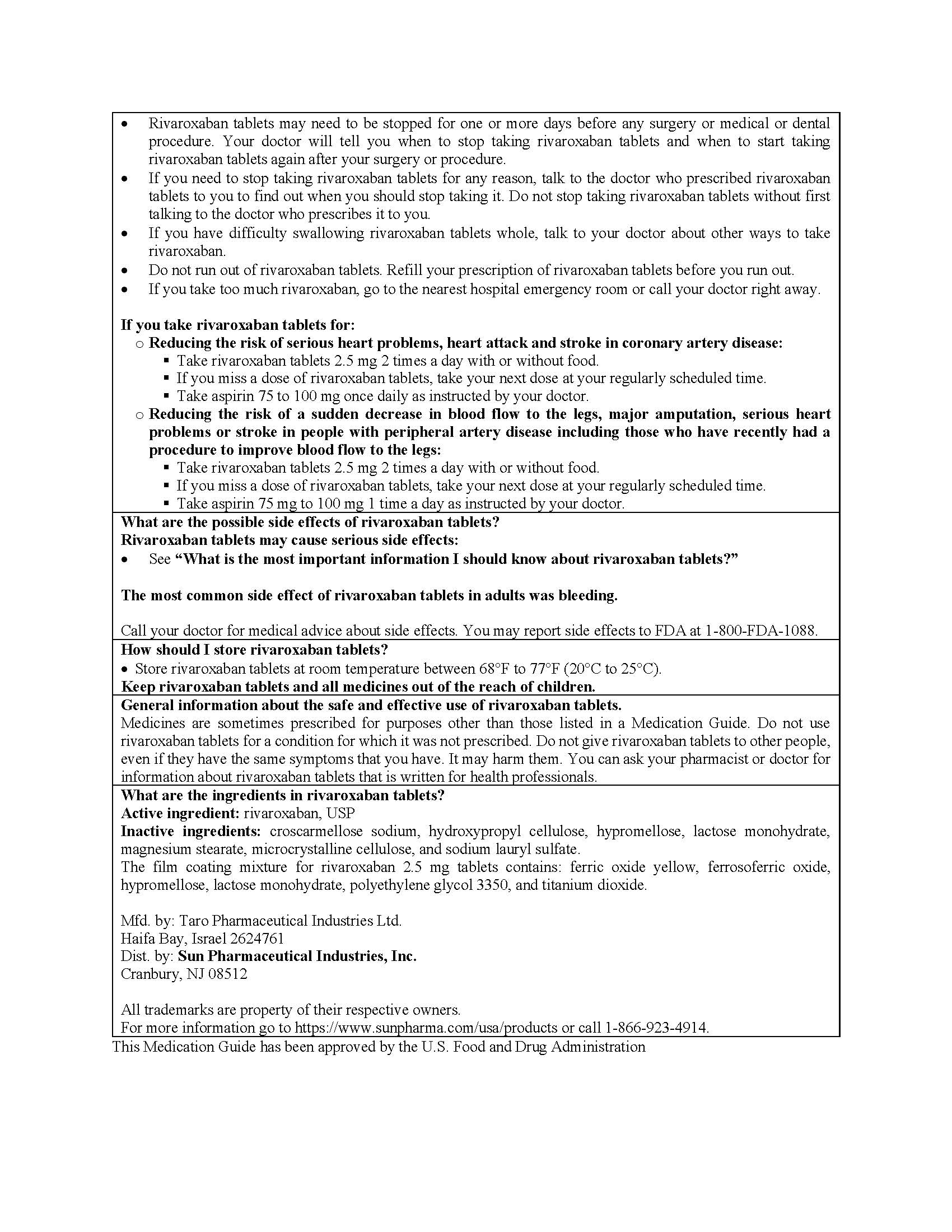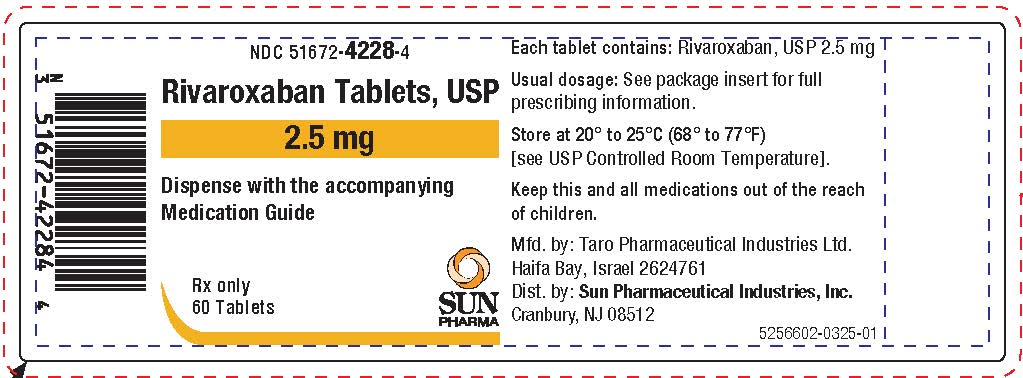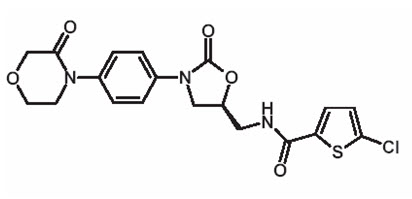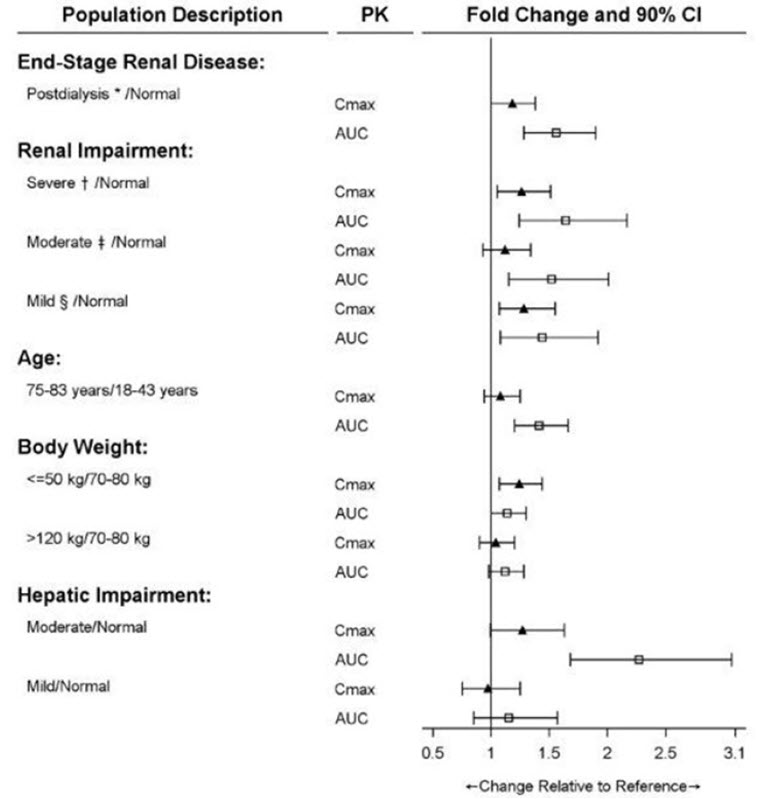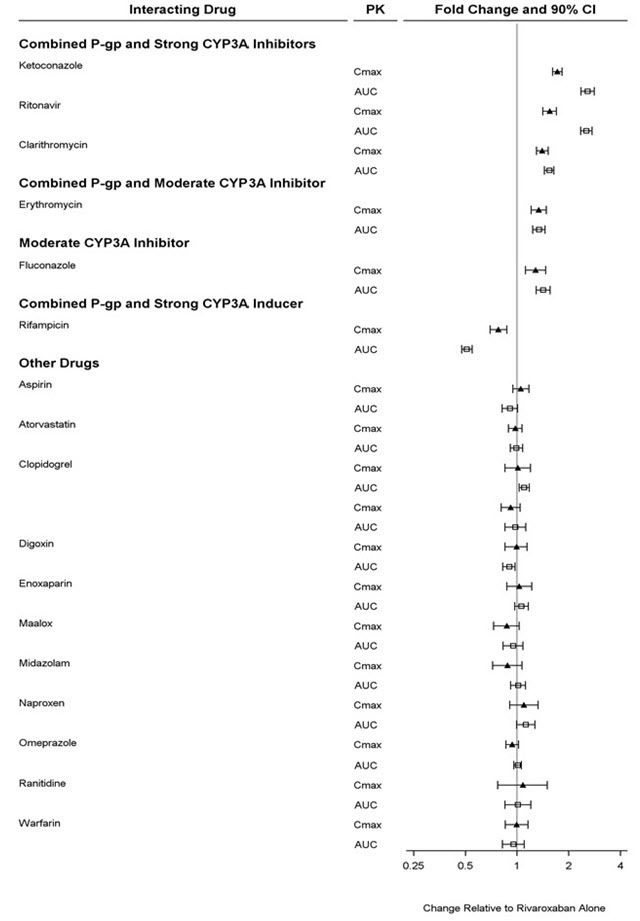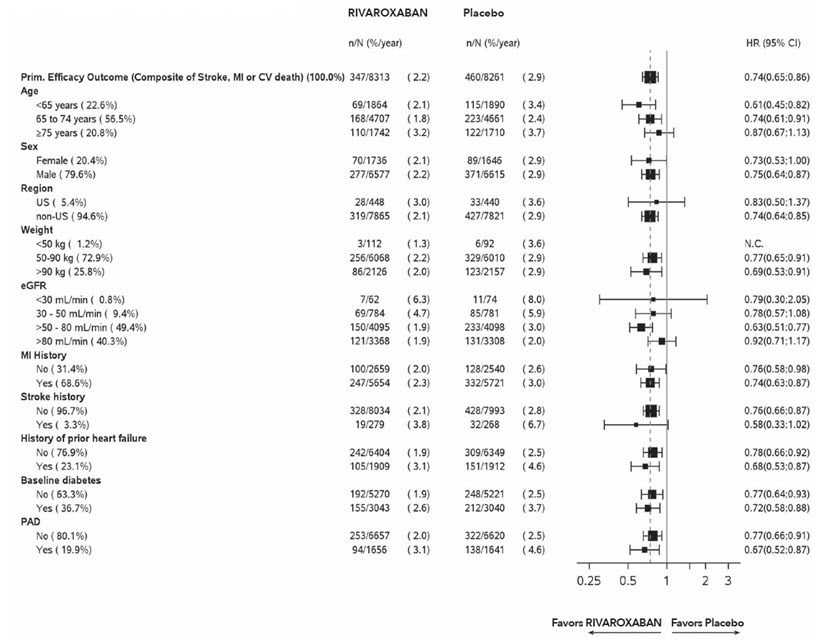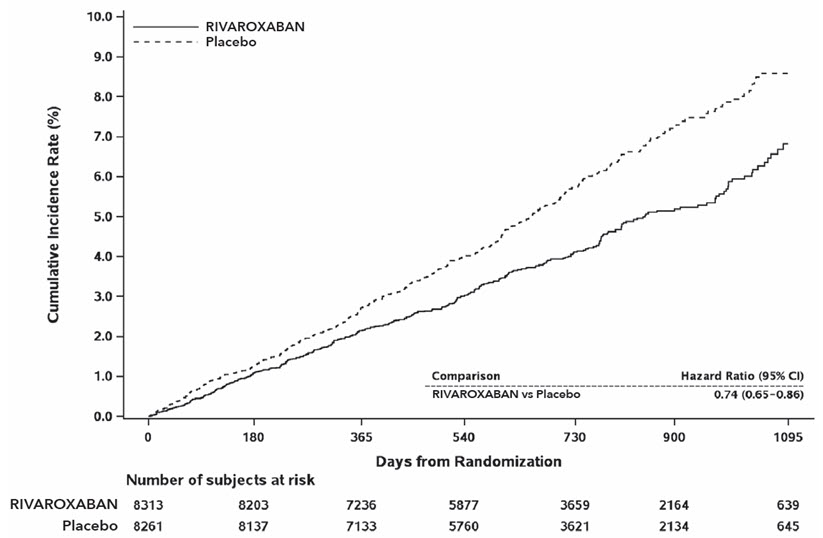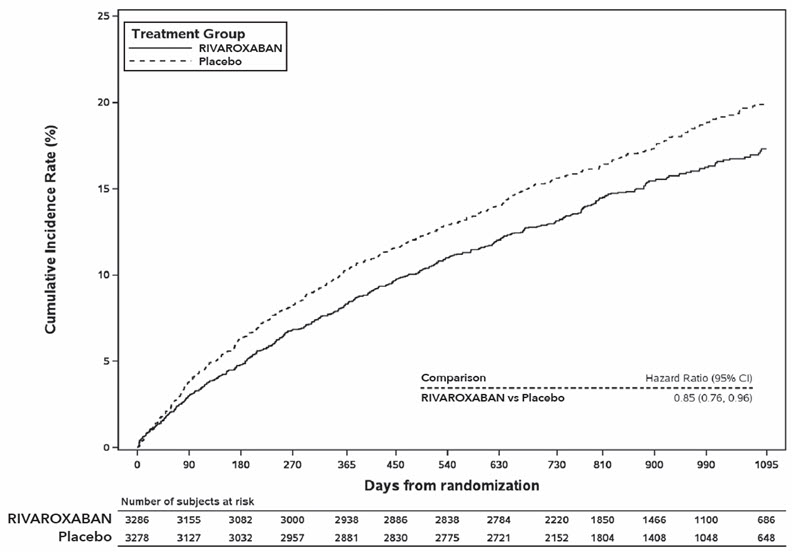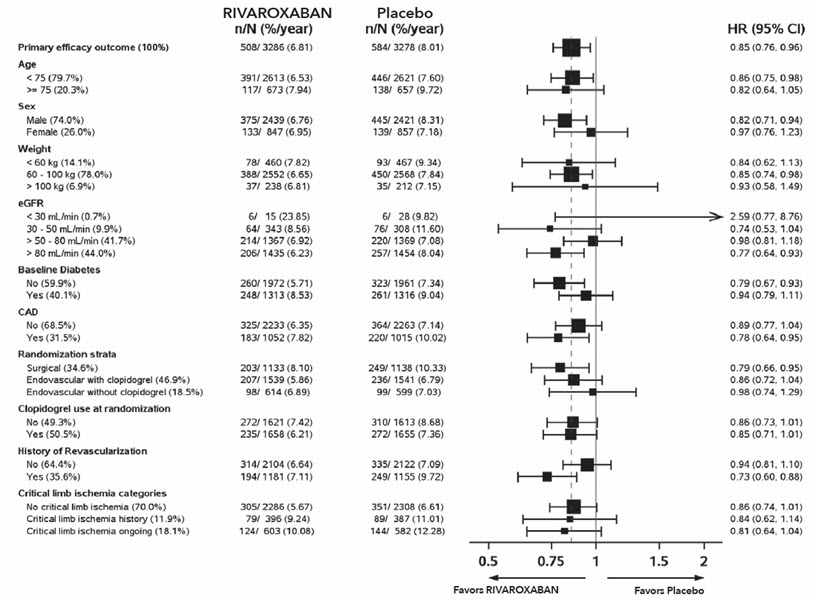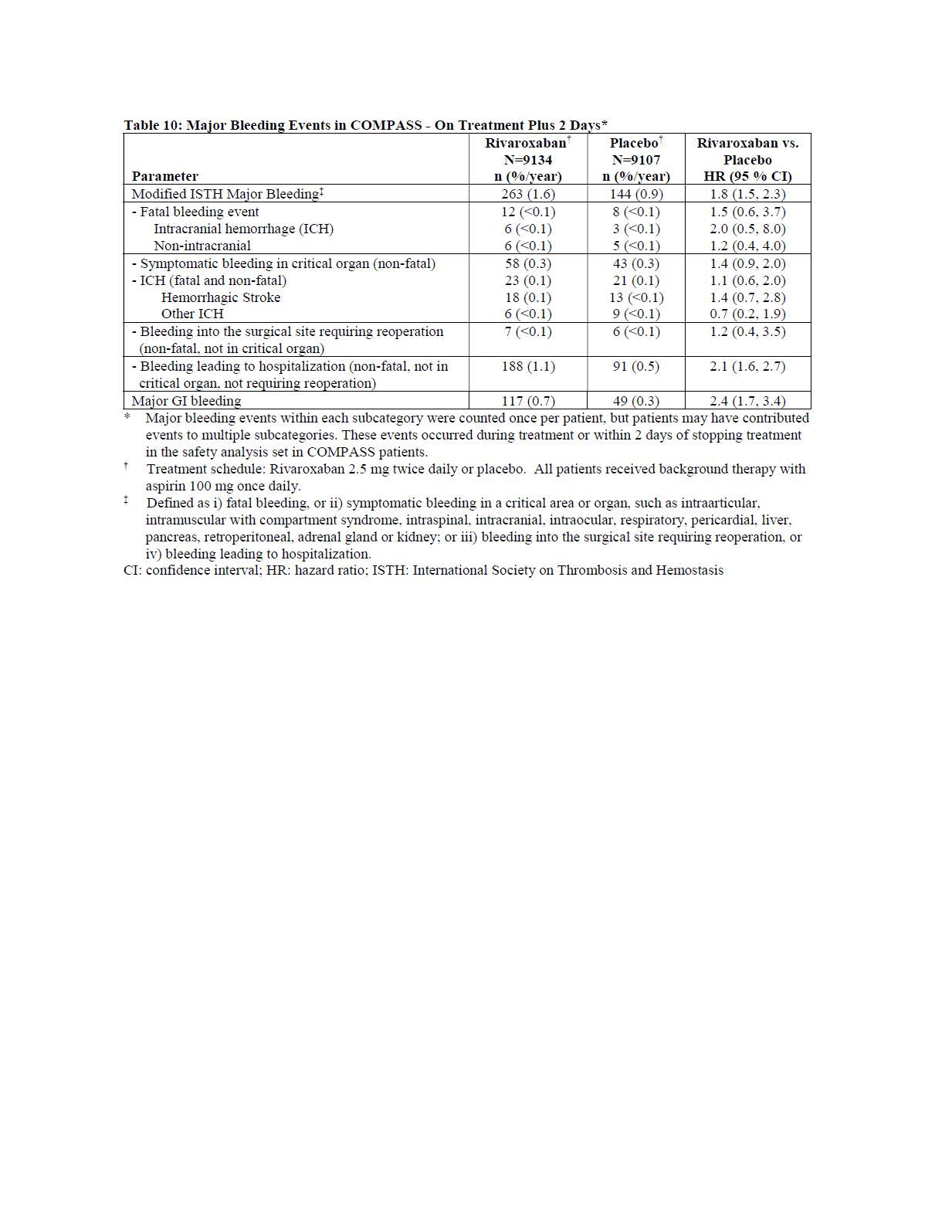 DRUG LABEL: Rivaroxaban
NDC: 51672-4228 | Form: TABLET, COATED
Manufacturer: Sun Pharmaceutical Industries, Inc.
Category: prescription | Type: HUMAN PRESCRIPTION DRUG LABEL
Date: 20251121

ACTIVE INGREDIENTS: RIVAROXABAN 2.5 mg/1 1
INACTIVE INGREDIENTS: MICROCRYSTALLINE CELLULOSE; SODIUM LAURYL SULFATE; CROSCARMELLOSE SODIUM; FERRIC OXIDE YELLOW; FERROSOFERRIC OXIDE; POLYETHYLENE GLYCOL 3350; TITANIUM DIOXIDE; HYDROXYPROPYL CELLULOSE (1600000 WAMW); HYPROMELLOSE, UNSPECIFIED; LACTOSE MONOHYDRATE; MAGNESIUM STEARATE

HIGHLIGHTS OF PRESCRIBING INFORMATION

These highlights do not include all the information needed to use RIVAROXABAN TABLETS safely and effectively. See full prescribing information for RIVAROXABAN TABLETS.
RIVAROXABAN tablets, for oral use
Initial U.S. Approval: 2011

WARNING: (A) PREMATURE DISCONTINUATION OF RIVAROXABAN INCREASES THE RISK OF THROMBOTIC EVENTS, (B) SPINAL/EPIDURAL HEMATOMA

WARNING: (A) PREMATURE DISCONTINUATION OF RIVAROXABAN TABLETS INCREASES THE RISK OF THROMBOTIC EVENTS, (B) SPINAL/EPIDURAL HEMATOMA

See full prescribing information for complete boxed warning.

(A) Premature discontinuation of rivaroxaban increases the risk of thrombotic events

Premature discontinuation of any oral anticoagulant, including rivaroxaban, increases the risk of thrombotic events. To reduce this risk, consider coverage with another anticoagulant if rivaroxaban is discontinued for a reason other than pathological bleeding or completion of a course of therapy. (2.3, 5.1)

(B) Spinal/epidural hematoma

Epidural or spinal hematomas have occurred in patients treated with rivaroxaban who are receiving neuraxial anesthesia or undergoing spinal puncture. These hematomas may result in long-term or permanent paralysis. (5.2, 5.3, 6.2)

Monitor patients frequently for signs and symptoms of neurological impairment and if observed, treat urgently. Consider the benefits and risks before neuraxial intervention in patients who are or who need to be anticoagulated. (5.3)

1 INDICATIONS AND USAGE

Rivaroxaban is a factor Xa inhibitor indicated:

- to reduce the risk of major cardiovascular events in patients with coronary artery disease (CAD) (1.7)
- to reduce the risk of major thrombotic vascular events in patients with peripheral artery disease (PAD), including patients after recent lower extremity revascularization due to symptomatic PAD (1.8)

2 DOSAGE AND ADMINISTRATION

- CAD or PAD: 2.5 mg orally twice daily with or without food, in combination with aspirin (75 to 100 mg) once daily (2.1)

3 DOSAGE FORMS AND STRENGTHS

- Tablets: 2.5 mg (3)

4 CONTRAINDICATIONS

- Active pathological bleeding (4)
- Severe hypersensitivity reaction to rivaroxaban (4)

5 WARNINGS AND PRECAUTIONS

- Risk of bleeding: Rivaroxaban can cause serious and fatal bleeding. An agent to reverse the activity of rivaroxaban is available. (5.2)
- Pregnancy-related hemorrhage: Use rivaroxaban with caution in pregnant women due to the potential for obstetric hemorrhage and/or emergent delivery. (5.7, 8.1)
- Prosthetic heart valves: Rivaroxaban use not recommended. (5.8)
- Increased Risk of Thrombosis in Patients with Triple Positive Antiphospholipid Syndrome: Rivaroxaban use not recommended. (5.10)

6 ADVERSE REACTIONS

- The most common adverse reaction (>5%) in adult patients was bleeding. (6.1)

To report SUSPECTED ADVERSE REACTIONS, contact Sun Pharmaceutical Industries, Inc. at 1-866-923-4914 or FDA at 1-800-FDA-1088 or www.fda.gov/medwatch.

7 DRUG INTERACTIONS

- Avoid combined P-gp and strong CYP3A inhibitors and inducers (7.2, 7.3)
- Anticoagulants: Avoid concomitant use (7.4)

8 USE IN SPECIFIC POPULATIONS

- Renal impairment: Avoid or adjust dose (8.6)
- Hepatic impairment: Avoid use in Child-Pugh B and C hepatic impairment or hepatic disease associated with coagulopathy (8.7)

RECENT MAJOR CHANGES

Warnings and Precautions (5.2) 06/2025

FULL PRESCRIBING INFORMATION

WARNING: (A) PREMATURE DISCONTINUATION OF RIVAROXABAN INCREASES THE RISK OF THROMBOTIC EVENTS, (B) SPINAL/EPIDURAL HEMATOMA

A. Premature discontinuation of rivaroxaban increases the risk of thrombotic events

Premature discontinuation of any oral anticoagulant, including rivaroxaban, increases the risk of thrombotic events. If anticoagulation with rivaroxaban is discontinued for a reason other than pathological bleeding or completion of a course of therapy, consider coverage with another anticoagulant [see Dosage and Administration (2.3, 2.4), Warnings and Precautions (5.1)] .

B. Spinal/epidural hematoma

Epidural or spinal hematomas have occurred in patients treated with rivaroxaban who are receiving neuraxial anesthesia or undergoing spinal puncture. These hematomas may result in long-term or permanent paralysis. Consider these risks when scheduling patients for spinal procedures. Factors that can increase the risk of developing epidural or spinal hematomas in these patients include:

- use of indwelling epidural catheters
- concomitant use of other drugs that affect hemostasis, such as non-steroidal anti-inflammatory drugs (NSAIDs), platelet inhibitors, other anticoagulants
- a history of traumatic or repeated epidural or spinal punctures
- a history of spinal deformity or spinal surgery
- optimal timing between the administration of rivaroxaban and neuraxial procedures is not known [see Warnings and Precautions (5.2, 5.3)and Adverse Reactions (6.2)] .

Monitor patients frequently for signs and symptoms of neurological impairment. If neurological compromise is noted, urgent treatment is necessary [see Warnings and Precautions (5.3)] .

Consider the benefits and risks before neuraxial intervention in patients anticoagulated or to be anticoagulated for thromboprophylaxis [see Warnings and Precautions (5.3)] .

1 INDICATIONS AND USAGE

1.7 Reduction of Risk of Major Cardiovascular Events in Patients with Coronary Artery Disease (CAD)

Rivaroxaban tablets, in combination with aspirin, are indicated to reduce the risk of major cardiovascular events (cardiovascular death, myocardial infarction, and stroke) in adult patients with coronary artery disease.

1.8 Reduction of Risk of Major Thrombotic Vascular Events in Patients with Peripheral Artery Disease (PAD), Including Patients after Lower Extremity Revascularization due to Symptomatic PAD

Rivaroxaban tablets, in combination with aspirin, are indicated to reduce the risk of major thrombotic vascular events (myocardial infarction, ischemic stroke, acute limb ischemia, and major amputation of a vascular etiology) in adult patients with PAD, including patients who have recently undergone a lower extremity revascularization procedure due to symptomatic PAD.

2 DOSAGE AND ADMINISTRATION

2.1 Recommended Dosage in Adults

Table 1: Recommended Dosage in Adults
Indication | Renal Considerations [Calculate CrCl based on actual weight. [See Warnings and Precautions (5.4) and Use in Specific Populations (8.6)]] | Dosage | Food/Timing
Reduction of Risk of Major Cardiovascular Events (CV Death, MI, and Stroke) in CAD | No dose adjustment needed based on CrCl | 2.5 mg twice daily, plus aspirin (75 to 100 mg) once daily | Take with or without food
Reduction of Risk of Major Thrombotic Vascular Events in PAD, Including Patients after Lower Extremity Revascularization due to Symptomatic PAD | No dose adjustment needed based on CrCl | 2.5 mg twice daily, plus aspirin (75 to 100 mg) once daily When starting therapy after a successful lower extremity revascularization procedure, initiate once hemostasis has been established. | Take with or without food

2.3 Switching to and from Rivaroxaban

Switching from Warfarin to Rivaroxaban– When switching patients from warfarin to rivaroxaban, discontinue warfarin and start rivaroxaban as soon as the International Normalized Ratio (INR) is below 3.0 in adults and below 2.5 in pediatric patients to avoid periods of inadequate anticoagulation.

Switching from Rivaroxaban to Warfarin–

- Adults:

No clinical trial data are available to guide converting patients from rivaroxaban to warfarin. Rivaroxaban affects INR, so INR measurements made during coadministration with warfarin may not be useful for determining the appropriate dose of warfarin. One approach is to discontinue rivaroxaban and begin both a parenteral anticoagulant and warfarin at the time the next dose of rivaroxaban would have been taken.

Once rivaroxaban is discontinued, INR testing may be done reliably 24 hours after the last dose.

Switching from Rivaroxaban to Anticoagulants other than Warfarin- For adult patients currently taking rivaroxaban and transitioning to an anticoagulant with rapid onset, discontinue rivaroxaban and give the first dose of the other anticoagulant (oral or parenteral) at the time that the next rivaroxaban dose would have been taken [see Drug Interactions (7.4)].

Switching from Anticoagulants other than Warfarin to Rivaroxaban- For adult patients currently receiving an anticoagulant other than warfarin, start rivaroxaban 0 to 2 hours prior to the next scheduled administration of the drug (e.g., low molecular weight heparin or non-warfarin oral anticoagulant) and omit administration of the other anticoagulant. For unfractionated heparin being administered by continuous infusion, stop the infusion and start rivaroxaban at the same time.

2.4 Discontinuation for Surgery and other Interventions

If anticoagulation must be discontinued to reduce the risk of bleeding with surgical or other procedures, rivaroxaban should be stopped at least 24 hours before the procedure to reduce the risk of bleeding [see Warnings and Precautions (5.2)] . In deciding whether a procedure should be delayed until 24 hours after the last dose of rivaroxaban, the increased risk of bleeding should be weighed against the urgency of intervention. Rivaroxaban should be restarted after the surgical or other procedures as soon as adequate hemostasis has been established, noting that the time to onset of therapeutic effect is short [see Warnings and Precautions (5.1)] . If oral medication cannot be taken during or after surgical intervention, consider administering a parenteral anticoagulant.

2.5 Missed Dose

Adults

- For patients receiving 2.5 mg twice daily: if a dose is missed, the patient should take a single 2.5 mg rivaroxaban dose as recommended at the next scheduled time.

On the following day, the patient should continue with their regular regimen.

2.6 Administration Options

For adult patients who are unable to swallow whole tablets, rivaroxaban tablets (2.5 mg) may be crushed and mixed with applesauce immediately prior to use and administered orally. Administration with food is not required for the 2.5 mg [see Clinical Pharmacology (12.3)] .

Administration of rivaroxaban tablets via nasogastric (NG) tube or gastric feeding tube:After confirming gastric placement of the tube, rivaroxaban tablets (2.5 mg) may be crushed and suspended in 50 mL of water and administered via an NG tube or gastric feeding tube. Since rivaroxaban absorption is dependent on the site of drug release, avoid administration of rivaroxaban distal to the stomach which can result in reduced absorption and thereby, reduced drug exposure. Enteral feeding is not required following administration of the 2.5 mg tablets [see Clinical Pharmacology (12.3)] .

Crushed rivaroxaban tablets (2.5 mg) are stable in water and in applesauce for up to 4 hours. An in vitrocompatibility study indicated that there is no adsorption of rivaroxaban from a water suspension of a crushed rivaroxaban tablet to PVC or silicone nasogastric (NG) tubing.

3 DOSAGE FORMS AND STRENGTHS

- 2.5 mg tablets: Round, light yellow, film-coated and debossed on one side with "□" and "2.5" on the other side

4 CONTRAINDICATIONS

Rivaroxaban tablets are contraindicated in patients with:

- active pathological bleeding [see Warnings and Precautions (5.2)]
- severe hypersensitivity reaction to rivaroxaban (e.g., anaphylactic reactions) [see Adverse Reactions (6.2)]

5 WARNINGS AND PRECAUTIONS

5.1 Increased Risk of Thrombotic Events after Premature Discontinuation

Premature discontinuation of any oral anticoagulant, including rivaroxaban, in the absence of adequate alternative anticoagulation increases the risk of thrombotic events. An increased rate of stroke was observed during the transition from rivaroxaban to warfarin in clinical trials in another indication in patients. If rivaroxaban is discontinued for a reason other than pathological bleeding or completion of a course of therapy, consider coverage with another anticoagulant [see Dosage and Administration (2.3, 2.4)] .

5.2 Risk of Bleeding

Rivaroxaban increases the risk of bleeding and can cause serious or fatal bleeding. In deciding whether to prescribe rivaroxaban to patients at increased risk of bleeding, the risk of thrombotic events should be weighed against the risk of bleeding.

Promptly evaluate any signs or symptoms of blood loss and consider the need for blood replacement. Discontinue rivaroxaban in patients with active pathological hemorrhage. The terminal elimination half-life of rivaroxaban is 5 to 9 hours in healthy subjects aged 20 to 45 years.

Concomitant use of other drugs that impair hemostasis increases the risk of bleeding. These include aspirin, P2Y12platelet inhibitors, dual antiplatelet therapy, other antithrombotic agents, fibrinolytic therapy, non-steroidal anti-inflammatory drugs (NSAIDs) [see Drug Interactions (7.4)] , selective serotonin reuptake inhibitors, and serotonin norepinephrine reuptake inhibitors.

Concomitant use of drugs that are known combined P-gp and strong CYP3A inhibitors increases rivaroxaban exposure and may increase bleeding risk [see Drug Interactions (7.2)] .

Risk of Hemorrhage in Acutely Ill Medical Patients at High Risk of Bleeding

Acutely ill medical patients with the following conditions are at increased risk of bleeding with the use of rivaroxaban for another indication: history of bronchiectasis, pulmonary cavitation, or pulmonary hemorrhage, active cancer (i.e., undergoing acute, in-hospital cancer treatment), active gastroduodenal ulcer in the three months prior to treatment, history of bleeding in the three months prior to treatment, or dual antiplatelet therapy. Rivaroxaban is not for use for another indication in these hospitalized, acutely ill medical patients at high risk of bleeding.

Reversal of Anticoagulant Effect

An agent to reverse the anti-factor Xa activity of rivaroxaban is available. Because of high plasma protein binding, rivaroxaban is not dialyzable [see Clinical Pharmacology (12.3)] . Protamine sulfate and vitamin K are not expected to affect the anticoagulant activity of rivaroxaban. Use of procoagulant reversal agents, such as prothrombin complex concentrate (PCC), activated prothrombin complex concentrate or recombinant factor VIIa, may be considered but has not been evaluated in clinical efficacy and safety studies. Monitoring for the anticoagulation effect of rivaroxaban using a clotting test (PT, INR or aPTT) or anti-factor Xa (FXa) activity is not recommended.

5.3 Spinal/Epidural Anesthesia or Puncture

When neuraxial anesthesia (spinal/epidural anesthesia) or spinal puncture is employed, patients treated with anticoagulant agents for prevention of thromboembolic complications are at risk of developing an epidural or spinal hematoma which can result in long-term or permanent paralysis [see Boxed Warning] .

To reduce the potential risk of bleeding associated with the concurrent use of rivaroxaban and epidural or spinal anesthesia/analgesia or spinal puncture, consider the pharmacokinetic profile of rivaroxaban [see Clinical Pharmacology (12.3)] . Placement or removal of an epidural catheter or lumbar puncture is best performed when the anticoagulant effect of rivaroxaban is low; however, the exact timing to reach a sufficiently low anticoagulant effect in each patient is not known.

An indwelling epidural or intrathecal catheter should not be removed before at least 2 half-lives have elapsed (i.e., 18 hours in young patients aged 20 to 45 years and 26 hours in elderly patients aged 60 to 76 years), after the last administration of rivaroxaban [see Clinical Pharmacology (12.3)] . The next rivaroxaban dose should not be administered earlier than 6 hours after the removal of the catheter. If traumatic puncture occurs, delay the administration of rivaroxaban for 24 hours.

Should the physician decide to administer anticoagulation in the context of epidural or spinal anesthesia/analgesia or lumbar puncture, monitor frequently to detect any signs or symptoms of neurological impairment, such as midline back pain, sensory and motor deficits (numbness, tingling, or weakness in lower limbs), bowel and/or bladder dysfunction. Instruct patients to immediately report if they experience any of the above signs or symptoms. If signs or symptoms of spinal hematoma are suspected, initiate urgent diagnosis and treatment including consideration for spinal cord decompression even though such treatment may not prevent or reverse neurological sequelae.

5.4 Use in Patients with Renal Impairment

Pediatric Patients

There are no clinical data in pediatric patients younger than 1 year with serum creatinine results above 97.5thpercentile; therefore, avoid the use of rivaroxaban in these patients [see Use in Specific Populations (8.6)] .

5.5 Use in Patients with Hepatic Impairment

No clinical data are available for adult patients with severe hepatic impairment.

Avoid use of rivaroxaban in patients with moderate (Child-Pugh B) and severe (Child-Pugh C) hepatic impairment or with any hepatic disease associated with coagulopathy since drug exposure and bleeding risk may be increased [see Use in Specific Populations (8.7)].

No clinical data are available in pediatric patients with hepatic impairment.

5.6 Use with P-gp and Strong CYP3A Inhibitors or Inducers

Avoid concomitant use of rivaroxaban with known combined P-gp and strong CYP3A inhibitors [see Drug Interactions (7.2)].

Avoid concomitant use of rivaroxaban with drugs that are known combined P-gp and strong CYP3A inducers [see Drug Interactions (7.3)].

5.7 Risk of Pregnancy-Related Hemorrhage

In pregnant women, rivaroxaban should be used only if the potential benefit justifies the potential risk to the mother and fetus. Rivaroxaban dosing in pregnancy has not been studied. The anticoagulant effect of rivaroxaban cannot be monitored with standard laboratory testing. Promptly evaluate any signs or symptoms suggesting blood loss (e.g., a drop in hemoglobin and/or hematocrit, hypotension, or fetal distress) [see Warnings and Precautions (5.2)and Use in Specific Populations (8.1)] .

5.8 Patients with Prosthetic Heart Valves

On the basis of the GALILEO study, use of rivaroxaban is not recommended in patients who have had transcatheter aortic valve replacement (TAVR) because patients randomized to rivaroxaban experienced higher rates of death and bleeding compared to those randomized to an anti-platelet regimen. The safety and efficacy of rivaroxaban have not been studied in patients with other prosthetic heart valves or other valve procedures. Use of rivaroxaban is not recommended in patients with prosthetic heart valves.

5.9 Acute PE in Hemodynamically Unstable Patients or Patients Who Require Thrombolysis or Pulmonary Embolectomy

Initiation of rivaroxaban is not recommended acutely as an alternative to unfractionated heparin in patients with pulmonary embolism who present with hemodynamic instability or who may receive thrombolysis or pulmonary embolectomy.

5.10 Increased Risk of Thrombosis in Patients with Triple Positive Antiphospholipid Syndrome

Direct-acting oral anticoagulants (DOACs), including rivaroxaban, are not recommended for use in patients with triple-positive antiphospholipid syndrome (APS). For patients with APS (especially those who are triple positive [positive for lupus anticoagulant, anticardiolipin, and anti-beta 2-glycoprotein I antibodies]), treatment with DOACs has been associated with increased rates of recurrent thrombotic events compared with vitamin K antagonist therapy.

6 ADVERSE REACTIONS

The following clinically significant adverse reactions are also discussed in other sections of the labeling:

- Increased Risk of Stroke After Discontinuation in Another Indication [see Boxed Warningand Warnings and Precautions (5.1)]
- Bleeding Risk [see Warnings and Precautions (5.2, 5.4, 5.5, 5.6, 5.7)]
- Spinal/Epidural Hematoma [see Boxed Warningand Warnings and Precautions (5.3)]

6.1 Clinical Trials Experience

Because clinical trials are conducted under widely varying conditions, adverse reaction rates observed in the clinical trials of a drug cannot be directly compared to rates in the clinical trials of another drug and may not reflect the rates observed in clinical practice.

Hemorrhage

The most common adverse reactions with rivaroxaban were bleeding complications [see Warnings and Precautions (5.2)] .

Reduction of Risk of Major Cardiovascular Events in Patients with CAD
In the COMPASS trial overall, the most frequent adverse reactions associated with permanent drug discontinuation
were bleeding events, with incidence rates of 2.7% for rivaroxaban 2.5 mg twice daily vs. 1.2% for placebo on
background therapy for all patients with aspirin 100 mg once daily. The incidences of important bleeding events in
the CAD and PAD populations in COMPASS were similar.
Table 10 shows the number of patients experiencing various types of major bleeding events in the COMPASS trial.

Reduction of Risk of Major Thrombotic Vascular Events in Patients with Peripheral Artery Disease (PAD), Including Patients after Lower Extremity Revascularization due to Symptomatic PAD

The incidence of premature permanent discontinuation due to bleeding events for rivaroxaban 2.5 mg twice daily vs. placebo on background therapy with aspirin 100 mg once daily in VOYAGER was 4.1% vs. 1.6% and in COMPASS PAD was 2.7% vs. 1.3%, respectively.

Table 11 shows the number of patients experiencing various types of TIMI (Thrombolysis in Myocardial Infarction) major bleeding events in the VOYAGER trial. The most common site of bleeding was gastrointestinal.

Table 11: Major Bleeding Events [Major bleeding events within each subcategory were counted once per patient, but patients may have contributed events to multiple subcategories.] in VOYAGER - On Treatment Plus 2 Days
 | Rivaroxaban [Treatment schedule: Rivaroxaban 2.5 mg twice daily or placebo. All patients received background therapy with aspirin 100 mg once daily.] N=3256 |  | Placebo N=3248 |  | Rivaroxaban vs. Placebo HR (95 % CI)
Parameter | n (%) | Event rate %/year | n (%) | Event rate %/year | Rivaroxaban vs. Placebo HR (95 % CI)
TIMI Major Bleeding (CABG/non-CABG) | 62 (1.9) | 0.96 | 44 (1.4) | 0.67 | 1.4 (1.0, 2.1)
Fatal bleeding | 6 (0.2) | 0.09 | 6 (0.2) | 0.09 | 1.0 (0.3, 3.2)
Intracranial bleeding | 13 (0.4) | 0.20 | 17 (0.5) | 0.26 | 0.8 (0.4, 1.6)
Clinically overt signs of hemorrhage associated with a drop in hemoglobin of ≥5 g/dL or drop in hematocrit of ≥15% | 46 (1.4) | 0.71 | 24 (0.7) | 0.36 | 1.9 (1.2, 3.2)
CABG: Coronary artery bypass graft; CI: confidence interval; HR: hazard ratio; TIMI: Thrombolysis in Myocardial Infarction Bleeding Criteria

6.2 Postmarketing Experience

The following adverse reactions have been identified during post-approval use of rivaroxaban. Because these reactions are reported voluntarily from a population of uncertain size, it is not always possible to reliably estimate their frequency or establish a causal relationship to drug exposure.

Blood and lymphatic system disorders:agranulocytosis, thrombocytopenia

Hepatobiliary disorders:jaundice, cholestasis, hepatitis (including hepatocellular injury)

Immune system disorders:hypersensitivity, anaphylactic reaction, anaphylactic shock, angioedema

Nervous system disorders:hemiparesis

Renal disorders:Anticoagulant-related nephropathy

Respiratory, thoracic and mediastinal disorders:Eosinophilic pneumonia

Skin and subcutaneous tissue disorders:Stevens-Johnson syndrome, drug reaction with eosinophilia and systemic symptoms (DRESS)

Injury, poisoning and procedural complications: Atraumatic splenic rupture

7 DRUG INTERACTIONS

7.1 General Inhibition and Induction Properties

Rivaroxaban is a substrate of CYP3A4/5, CYP2J2, and the P-gp and ATP-binding cassette G2 (ABCG2) transporters. Combined P-gp and strong CYP3A inhibitors increase exposure to rivaroxaban and may increase the risk of bleeding. Combined P-gp and strong CYP3A inducers decrease exposure to rivaroxaban and may increase the risk of thromboembolic events.

7.2 Drugs that Inhibit Cytochrome P450 3A Enzymes and Drug Transport Systems

Interaction with Combined P-gp and Strong CYP3A Inhibitors

Avoid concomitant administration of rivaroxaban with known combined P-gp and strong CYP3A inhibitors (e.g., ketoconazole and ritonavir) [see Warnings and Precautions (5.6)and Clinical Pharmacology (12.3)] .

Although clarithromycin is a combined P-gp and strong CYP3A inhibitor, pharmacokinetic data suggests that no precautions are necessary with concomitant administration with rivaroxaban as the change in exposure is unlikely to affect the bleeding risk [see Clinical Pharmacology (12.3)] .

Interaction with Combined P-gp and Moderate CYP3A Inhibitors in Patients with Renal Impairment

Rivaroxaban should not be used in patients with CrCl 15 to <80 mL/min who are receiving concomitant combined P-gp and moderate CYP3A inhibitors (e.g., erythromycin) unless the potential benefit justifies the potential risk [see Warnings and Precautions (5.4)and Clinical Pharmacology (12.3)] .

7.3 Drugs that Induce Cytochrome P450 3A Enzymes and Drug Transport Systems

Avoid concomitant use of rivaroxaban with drugs that are combined P-gp and strong CYP3A inducers (e.g., carbamazepine, phenytoin, rifampin, St. John's wort) [see Warnings and Precautions (5.6)and Clinical Pharmacology (12.3)] .

7.4 Anticoagulants and NSAIDs/Aspirin

Coadministration of enoxaparin, warfarin, aspirin, clopidogrel and chronic NSAID use may increase the risk of bleeding [see Clinical Pharmacology (12.3)] .

Avoid concurrent use of rivaroxaban with other anticoagulants due to increased bleeding risk unless benefit outweighs risk. Promptly evaluate any signs or symptoms of blood loss if patients are treated concomitantly with aspirin, other platelet aggregation inhibitors, or NSAIDs [see Warnings and Precautions (5.2)] .

8 USE IN SPECIFIC POPULATIONS

8.1 Pregnancy

Risk Summary

The limited available data on rivaroxaban in pregnant women are insufficient to inform a drug-associated risk of adverse developmental outcomes. Use rivaroxaban with caution in pregnant patients because of the potential for pregnancy related hemorrhage and/or emergent delivery. The anticoagulant effect of rivaroxaban cannot be reliably monitored with standard laboratory testing. Consider the benefits and risks of rivaroxaban for the mother and possible risks to the fetus when prescribing rivaroxaban to a pregnant woman [see Warnings and Precautions (5.2, 5.7)] .

Adverse outcomes in pregnancy occur regardless of the health of the mother or the use of medications. The estimated background risk of major birth defects and miscarriage for the indicated populations is unknown. In the U.S. general population, the estimated background risk of major birth defects and miscarriage in clinically recognized pregnancies is 2 to 4% and 15 to 20%, respectively.

Clinical Considerations

Disease-Associated Maternal and/or Embryo/Fetal Risk

Pregnancy is a risk factor for venous thromboembolism and that risk is increased in women with inherited or acquired thrombophilias. Pregnant women with thromboembolic disease have an increased risk of maternal complications including pre-eclampsia. Maternal thromboembolic disease increases the risk for intrauterine growth restriction, placental abruption and early and late pregnancy loss.

Fetal/Neonatal Adverse Reactions

Based on the pharmacologic activity of Factor Xa inhibitors and the potential to cross the placenta, bleeding may occur at any site in the fetus and/or neonate.

Labor or Delivery

All patients receiving anticoagulants, including pregnant women, are at risk for bleeding and this risk may be increased during labor or delivery [see Warnings and Precautions (5.7)] . The risk of bleeding should be balanced with the risk of thrombotic events when considering the use of rivaroxaban in this setting.

Data

Human Data

There are no adequate or well-controlled studies of rivaroxaban in pregnant women, and dosing for pregnant women has not been established. Post-marketing experience is currently insufficient to determine a rivaroxaban-associated risk for major birth defects or miscarriage. In an in vitroplacenta perfusion model, unbound rivaroxaban was rapidly transferred across the human placenta.

Animal Data

Rivaroxaban crosses the placenta in animals. Rivaroxaban increased fetal toxicity (increased resorptions, decreased number of live fetuses, and decreased fetal body weight) when pregnant rabbits were given oral doses of ≥10 mg/kg rivaroxaban during the period of organogenesis. This dose corresponds to about 4 times the human exposure of unbound drug, based on AUC comparisons at the highest recommended human dose of 20 mg/day. Fetal body weights decreased when pregnant rats were given oral doses of 120 mg/kg during the period of organogenesis. This dose corresponds to about 14 times the human exposure of unbound drug. In rats, peripartal maternal bleeding and maternal and fetal death occurred at the rivaroxaban dose of 40 mg/kg (about 6 times maximum human exposure of the unbound drug at the human dose of 20 mg/day).

8.2 Lactation

Risk Summary

Rivaroxaban has been detected in human milk. There are insufficient data to determine the effects of rivaroxaban on the breastfed child or on milk production. Rivaroxaban and/or its metabolites were present in the milk of rats. The developmental and health benefits of breastfeeding should be considered along with the mother's clinical need for rivaroxaban and any potential adverse effects on the breastfed infant from rivaroxaban or from the underlying maternal condition (see Data) .

Data

Animal Data

Following a single oral administration of 3 mg/kg of radioactive [^14C]-rivaroxaban to lactating rats between Day 8 to 10 postpartum, the concentration of total radioactivity was determined in milk samples collected up to 32 hours post-dose. The estimated amount of radioactivity excreted with milk within 32 hours after administration was 2.1% of the maternal dose.

8.3 Females and Males of Reproductive Potential

Females of reproductive potential requiring anticoagulation should discuss pregnancy planning with their physician.

The risk of clinically significant uterine bleeding, potentially requiring gynecological surgical interventions, identified with oral anticoagulants including rivaroxaban should be assessed in females of reproductive potential and those with abnormal uterine bleeding.

8.4 Pediatric Use

For the rivaroxaban 2.5 mg tablets, there are no safety, efficacy, pharmacokinetic and pharmacodynamic data to support the use in pediatric patients. Therefore, rivaroxaban 2.5 mg tablets are not recommended for use in pediatric patients.

Although not all adverse reactions identified in the adult population have been observed in clinical trials of children and adolescent patients, the same warnings and precautions for adults should be considered for children and adolescents.

8.5 Geriatric Use

Of the total number of adult patients in clinical trials for the approved indications of rivaroxaban (N=64,943 patients), 64 percent were 65 years and over, with 27 percent 75 years and over. In clinical trials the efficacy of rivaroxaban in the elderly (65 years or older) was similar to that seen in patients younger than 65 years. Both thrombotic and bleeding event rates were higher in these older patients [see Clinical Pharmacology (12.3)and Clinical Studies (14)] .

8.6 Renal Impairment

In pharmacokinetic studies, compared to healthy adult subjects with normal creatinine clearance, rivaroxaban exposure increased by approximately 44 to 64% in adult subjects with renal impairment. Increases in pharmacodynamic effects were also observed [see Clinical Pharmacology (12.3)] .

Reduction of Risk of Major Cardiovascular Events in Patients with CAD and Reduction of Risk of Major Thrombotic Vascular Events in Patients with PAD, Including Patients After Recent Lower Extremity Revascularization due to Symptomatic PAD

Patients with Chronic Kidney Disease not on Dialysis

Patients with a CrCl <15 mL/min at screening were excluded from COMPASS and VOYAGER, and limited data are available for patients with a CrCl of 15 to 30 mL/min. In patients with CrCl <30 mL/min, a dose of 2.5 mg rivaroxaban twice daily is expected to give an exposure similar to that in patients with moderate renal impairment (CrCl 30 to <50 mL/min) [see Clinical Pharmacology (12.3)] , whose efficacy and safety outcomes were similar to those with preserved renal function.

Patients with End-Stage Renal Disease on Dialysis

No clinical outcome data is available for the use of rivaroxaban with aspirin in patients with ESRD on dialysis since these patients were not enrolled in COMPASS or VOYAGER. In patients with ESRD maintained on intermittent hemodialysis, administration of rivaroxaban 2.5 mg twice daily will result in concentrations of rivaroxaban and pharmacodynamic activity similar to those observed in moderate renal impaired patients in the COMPASS study [see Clinical Pharmacology (12.2, 12.3)] . It is not known whether these concentrations will lead to similar CV risk reduction and bleeding risk in patients with ESRD on dialysis as was seen in COMPASS.

Pediatric Use

There are no clinical data in pediatric patients younger than 1 year with serum creatinine results above 97.5thpercentile; therefore, avoid the use of rivaroxaban in these patients [see Dosage and Administration (2.2)] .

8.7 Hepatic Impairment

In a pharmacokinetic study, compared to healthy adult subjects with normal liver function, AUC increases of 127% were observed in adult subjects with moderate hepatic impairment (Child-Pugh B).

The safety or PK of rivaroxaban in patients with severe hepatic impairment (Child-Pugh C) has not been evaluated [see Clinical Pharmacology (12.3)] .

Avoid the use of rivaroxaban in patients with moderate (Child-Pugh B) and severe (Child-Pugh C) hepatic impairment or with any hepatic disease associated with coagulopathy.

No clinical data are available in pediatric patients with hepatic impairment.

10 OVERDOSAGE

Overdose of rivaroxaban may lead to hemorrhage. Discontinue rivaroxaban and initiate appropriate therapy if bleeding complications associated with overdosage occur. Rivaroxaban systemic exposure is not further increased at single doses >50 mg due to limited absorption. The use of activated charcoal to reduce absorption in case of rivaroxaban overdose may be considered. Due to the high plasma protein binding, rivaroxaban is not dialyzable [see Warnings and Precautions (5.2)and Clinical Pharmacology (12.3)] . Partial reversal of laboratory anticoagulation parameters may be achieved with use of plasma products. An agent to reverse the anti-factor Xa activity of rivaroxaban is available.

11 DESCRIPTION

Rivaroxaban, USP, a factor Xa (FXa) inhibitor, is the active ingredient in rivaroxaban tablets, USP with the chemical name 5-Chloro-N-({(5S)-2-oxo-3-[4-(3-oxo-4-morpholinyl)phenyl]-1,3-oxazolidin-5-yl}methyl)-2-thiophenecarboxamide. The molecular formula of rivaroxaban, USP is C19H18ClN3O5S and the molecular weight is 435.89. The structural formula is:

Rivaroxaban, USP is a pure (S)-enantiomer. It is an odorless, non-hygroscopic, white to yellowish powder. Rivaroxaban, USP is only slightly soluble in organic solvents (e.g., acetone, polyethylene glycol 400) and is practically insoluble in water and aqueous media.

Each rivaroxaban tablet, USP contains 2.5 mg of rivaroxaban, USP. The inactive ingredients of rivaroxaban tablets, USP are: croscarmellose sodium, hydroxypropyl cellulose, hypromellose, lactose monohydrate, magnesium stearate, microcrystalline cellulose, and sodium lauryl sulfate. Additionally, the film coating mixture for rivaroxaban 2.5 mg tablets, USP contains: ferric oxide yellow, ferrosoferric oxide, hypromellose, lactose monohydrate, polyethylene glycol 3350, and titanium dioxide.

12 CLINICAL PHARMACOLOGY

12.1 Mechanism of Action

Rivaroxaban is a selective inhibitor of FXa. It does not require a cofactor (such as Anti-thrombin III) for activity. Rivaroxaban inhibits free FXa and prothrombinase activity. Rivaroxaban has no direct effect on platelet aggregation, but indirectly inhibits platelet aggregation induced by thrombin. By inhibiting FXa, rivaroxaban decreases thrombin generation.

12.2 Pharmacodynamics

Rivaroxaban produces dose-dependent inhibition of FXa activity. Clotting tests, such as prothrombin time (PT), activated partial thromboplastin time (aPTT) and HepTest®, are also prolonged dose-dependently. In children treated with rivaroxaban, the correlation between anti-factor Xa to plasma concentrations is linear with a slope close to 1.

Monitoring for anticoagulation effect of rivaroxaban using anti-FXa activity or a clotting test is not recommended.

Specific Populations

Renal Impairment

The relationship between systemic exposure and pharmacodynamic activity of rivaroxaban was altered in adult subjects with renal impairment relative to healthy control subjects [see Use in Specific Populations (8.6)] .

Table 18: Percentage Increase in Rivaroxaban PK and PD Measures in Adult Subjects with Renal Impairment Relative to Healthy Subjects from Clinical Pharmacology Studies
Measure | Parameter | Creatinine Clearance (mL/min)
Measure | Parameter | 50 to 79 | 30 to 49 | 15 to 29 | ESRD (on dialysis) [Separate stand-alone study.] | ESRD (post-dialysis)
Exposure | AUC | 44 | 52 | 64 | 47 | 56
FXa Inhibition | AUEC | 50 | 86 | 100 | 49 | 33
PT Prolongation | AUEC | 33 | 116 | 144 | 112 | 158
PT = Prothrombin time; FXa = Coagulation factor Xa; AUC = Area under the plasma concentration-time curve; AUEC = Area under the effect-time curve

Hepatic Impairment

Anti-Factor Xa activity was similar in adult subjects with normal hepatic function and in mild hepatic impairment (Child-Pugh A class). There is no clear understanding of the impact of hepatic impairment beyond this degree on the coagulation cascade and its relationship to efficacy and safety.

12.3 Pharmacokinetics

Absorption

The absolute bioavailability of rivaroxaban is dose-dependent. For the 2.5 mg dose, it is estimated to be 80% to 100% and is not affected by food. Rivaroxaban 2.5 mg tablets can be taken with or without food.

The maximum concentrations (Cmax) of rivaroxaban appear 2 to 4 hours after tablet intake. The pharmacokinetics of rivaroxaban were not affected by drugs altering gastric pH. Coadministration of rivaroxaban (30 mg single dose) with the H2-receptor antagonist ranitidine (150 mg twice daily), the antacid aluminum hydroxide/magnesium hydroxide (10 mL) or rivaroxaban (20 mg single dose) with the PPI omeprazole (40 mg once daily) did not show an effect on the bioavailability and exposure of rivaroxaban (see Figure 3).

Absorption of rivaroxaban is dependent on the site of drug release in the GI tract. A 29% and 56% decrease in AUC and Cmaxcompared to tablet was reported when rivaroxaban granulate is released in the proximal small intestine. Exposure is further reduced when drug is released in the distal small intestine, or ascending colon. Avoid administration of rivaroxaban distal to the stomach which can result in reduced absorption and related drug exposure.

In a study with 44 healthy subjects, both mean AUC and Cmaxvalues for 20 mg rivaroxaban administered orally as a crushed tablet mixed in applesauce were comparable to that after the whole tablet. However, for the crushed tablet suspended in water and administered via an NG tube followed by a liquid meal, only mean AUC was comparable to that after the whole tablet, and Cmaxwas 18% lower.

Distribution

Protein binding of rivaroxaban in human plasma is approximately 92% to 95%, with albumin being the main binding component. The steady-state volume of distribution in healthy subjects is approximately 50 L.

Metabolism

Approximately 51% of an orally administered [^14C]-rivaroxaban dose was recovered as inactive metabolites in urine (30%) and feces (21%). Oxidative degradation catalyzed by CYP3A4/5 and CYP2J2 and hydrolysis are the major sites of biotransformation. Unchanged rivaroxaban was the predominant moiety in plasma with no major or active circulating metabolites.

Excretion

In a Phase 1 study, following the administration of [^14C]-rivaroxaban, approximately one-third (36%) was recovered as unchanged drug in the urine and 7% was recovered as unchanged drug in feces. Unchanged drug is excreted into urine, mainly via active tubular secretion and to a lesser extent via glomerular filtration (approximate 5:1 ratio). Rivaroxaban is a substrate of the efflux transporter proteins P-gp and ABCG2 (also abbreviated BCRP). Rivaroxaban's affinity for influx transporter proteins is unknown.

Rivaroxaban is a low-clearance drug, with a systemic clearance of approximately 10 L/hr in healthy volunteers following intravenous administration. The terminal elimination half-life of rivaroxaban is 5 to 9 hours in healthy subjects aged 20 to 45 years.

Specific Populations

The effects of level of renal impairment, age, body weight, and level of hepatic impairment on the pharmacokinetics of rivaroxaban are summarized in Figure 2.

Figure 2: Effect of Specific Adult Populations on the Pharmacokinetics of Rivaroxaban

* ESRD subjects maintained with chronic and stable hemodialysis; reported PK findings are following single dose of rivaroxaban post hemodialysis.
†Creatinine clearance 15 to 29 mL/min.
‡Creatinine clearance 30 to 49 mL/min.
§Creatinine clearance 50 to 79 mL/min.
[See Dosage and Administration (2.1)]

Gender

Gender did not influence the pharmacokinetics or pharmacodynamics of rivaroxaban.

Race

Healthy Japanese subjects were found to have 20 to 40% on average higher exposures compared to other ethnicities including Chinese. However, these differences in exposure are reduced when values are corrected for body weight.

Hemodialysis in ESRD subjects:Systemic exposure to rivaroxaban administered as a single 15 mg dose in ESRD subjects dosed 3 hours after the completion of a 4-hour hemodialysis session (post-dialysis) is 56% higher when compared to subjects with normal renal function (see Table 18). The systemic exposure to rivaroxaban administered 2 hours prior to a 4-hour hemodialysis session with a dialysate flow rate of 600 mL/min and a blood flow rate in the range of 320 mL/min to 400 mL/min is 47% higher compared to those with normal renal function. The extent of the increase is similar to the increase in patients with CrCl 15 mL/min to 50 mL/min taking rivaroxaban 15 mg. Hemodialysis had no significant impact on rivaroxaban exposure. Protein binding was similar (86% to 89%) in healthy controls and ESRD subjects in this study.

Pediatric Patients:Limited clinical data are available in children 1 year or older with moderate or severe renal impairment (eGFR <50 mL/min/1.73 m^2) or in children younger than 1 year with serum creatinine results above 97.5thpercentile [see Use in Specific Populations (8.6)] .

Elderly

The terminal elimination half-life is 11 to 13 hours in the elderly subjects aged 60 to 76 years [see Use in Specific Populations (8.5)] .

Pediatric Patients

The rate and extent of absorption were similar between the tablet and suspension. After repeated administration of rivaroxaban for the treatment of another indication, the Cmaxof rivaroxaban in plasma was observed at median times of 1.5 to 2.2 hours in subjects who ranged from birth to less than 18 years of age.

In children who were 6 months to 9 years of age, in vitroplasma protein binding of rivaroxaban is approximately 90%.

The half-life of rivaroxaban in plasma of pediatric patients treated for another indication decreased with decreasing age. Mean half-life values were 4.2 hours in adolescents, 3 hours in children 2 to 12 years of age, 1.9 hours in children 0.5 to <2 years of age, and 1.6 hours in children <0.5 years of age.

An exploratory analysis in pediatric patients treated for another indication did not reveal relevant differences in rivaroxaban exposure based on gender or race.

Renal Impairment

The safety and pharmacokinetics of single-dose rivaroxaban (10 mg) were evaluated in a study in healthy subjects [CrCl ≥80 mL/min (n=8)] and in subjects with varying degrees of renal impairment (see Figure 2). Compared to healthy subjects with normal creatinine clearance, rivaroxaban exposure increased in subjects with renal impairment. Increases in pharmacodynamic effects were also observed [see Use in Specific Populations (8.6)] .

Hepatic Impairment

The safety and pharmacokinetics of single-dose rivaroxaban (10 mg) were evaluated in a study in healthy adult subjects (n=16) and adult subjects with varying degrees of hepatic impairment (see Figure 2). No patients with severe hepatic impairment (Child-Pugh C) were studied. Compared to healthy subjects with normal liver function, significant increases in rivaroxaban exposure were observed in subjects with moderate hepatic impairment (Child-Pugh B) (see Figure 2). Increases in pharmacodynamic effects were also observed [see Use in Specific Populations (8.7)] .

No clinical data are available in pediatric patients with hepatic impairment.

Drug Interactions

In vitrostudies indicate that rivaroxaban neither inhibits the major cytochrome P450 enzymes CYP1A2, 2C8, 2C9, 2C19, 2D6, 2J2, and 3A nor induces CYP1A2, 2B6, 2C19, or 3A. In vitrodata also indicates a low rivaroxaban inhibitory potential for P-gp and ABCG2 transporters.

The effects of coadministered drugs on the pharmacokinetics of rivaroxaban exposure are summarized in Figure 3 [see Drug Interactions (7)] .

Figure 3: Effect of Coadministered Drugs on the Pharmacokinetics of Rivaroxaban in Adults

Anticoagulants

In a drug interaction study, single doses of enoxaparin (40 mg subcutaneous) and rivaroxaban (10 mg) given concomitantly resulted in an additive effect on anti-factor Xa activity. In another study, single doses of warfarin (15 mg) and rivaroxaban (5 mg) resulted in an additive effect on factor Xa inhibition and PT. Neither enoxaparin nor warfarin affected the pharmacokinetics of rivaroxaban (see Figure 3).

NSAIDs/Aspirin

NSAIDs are known to increase bleeding, and bleeding risk may be increased when NSAIDs are used concomitantly with rivaroxaban. Neither naproxen nor aspirin affected the pharmacokinetics of rivaroxaban (see Figure 3).

Clopidogrel

In two drug interaction studies where clopidogrel (300 mg loading dose followed by 75 mg daily maintenance dose) and rivaroxaban (15 mg single dose) were coadministered in healthy subjects, an increase in bleeding time to 45 minutes was observed in approximately 45% and 30% of subjects in these studies, respectively. The change in bleeding time was approximately twice the maximum increase seen with either drug alone. There was no change in the pharmacokinetics of either drug.

Drug-Disease Interactions with Drugs that Inhibit Cytochrome P450 3A Enzymes and Drug Transport Systems

In a pharmacokinetic trial, rivaroxaban was administered as a single dose in subjects with mild (CrCl = 50 to 79 mL/min) or moderate renal impairment (CrCl = 30 to 49 mL/min) receiving multiple doses of erythromycin (a combined P-gp and moderate CYP3A inhibitor). Compared to rivaroxaban administered alone in subjects with normal renal function (CrCl >80 mL/min), subjects with mild and moderate renal impairment concomitantly receiving erythromycin reported a 76% and 99% increase in AUCinfand a 56% and 64% increase in Cmax, respectively. Similar trends in pharmacodynamic effects were also observed.

12.6 QT/QTc Prolongation

In a thorough QT study in healthy men and women aged 50 years and older, no QTc prolonging effects were observed for rivaroxaban (15 mg and 45 mg, single-dose).

13 NON-CLINICAL TOXICOLOGY

13.1 Carcinogenesis, Mutagenesis, Impairment of Fertility

Rivaroxaban was not carcinogenic when administered by oral gavage to mice or rats for up to 2 years. The systemic exposures (AUCs) of unbound rivaroxaban in male and female mice at the highest dose tested (60 mg/kg/day) were 1- and 2-times, respectively, the human exposure of unbound drug at the human dose of 20 mg/day. Systemic exposures of unbound drug in male and female rats at the highest dose tested (60 mg/kg/day) were 2- and 4-times, respectively, the human exposure.

Rivaroxaban was not mutagenic in bacteria (Ames-Test) or clastogenic in V79 Chinese hamster lung cells in vitroor in the mouse micronucleus test in vivo.

No impairment of fertility was observed in male or female rats when given up to 200 mg/kg/day of rivaroxaban orally. This dose resulted in exposure levels, based on the unbound AUC, at least 13 times the exposure in humans given 20 mg rivaroxaban daily.

14 CLINICAL STUDIES

14.6 Reduction of Risk of Major Cardiovascular Events in Patients with CAD

The evidence for the efficacy and safety of rivaroxaban for the reduction in the risk of stroke, myocardial infarction, or cardiovascular death in patients with coronary artery disease (CAD) or peripheral artery disease (PAD) was derived from the double-blind, placebo-controlled Cardiovascular Outco Mes for People using Anticoagulation Strategie Strial (COMPASS) [NCT10776424]. A total of 27,395 patients were evenly randomized to rivaroxaban 2.5 mg orally twice daily plus aspirin 100 mg once daily, rivaroxaban 5 mg orally twice daily alone, or aspirin 100 mg once daily alone. Because the 5 mg dose alone was not superior to aspirin alone, only the data concerning the 2.5 mg dose plus aspirin are discussed below.

Patients with established CAD or PAD were eligible. Patients with CAD who were younger than 65 years of age were also required to have documentation of atherosclerosis involving at least two vascular beds or to have at least two additional cardiovascular risk factors (current smoking, diabetes mellitus, an estimated glomerular filtration rate [eGFR] <60 mL per minute, heart failure, or non-lacunar ischemic stroke ≥1 month earlier). Patients with PAD were either symptomatic with ankle brachial index <0.90 or had asymptomatic carotid artery stenosis ≥50%, a previous carotid revascularization procedure, or established ischemic disease of one or both lower extremities. Patients were excluded for use of dual antiplatelet, other non-aspirin antiplatelet, or oral anticoagulant therapies, ischemic, non-lacunar stroke within 1 month, hemorrhagic or lacunar stroke at any time, or eGFR <15 mL/min.

The mean age was 68 years and 21% of the subject population were ≥75 years. Of the included patients, 91% had CAD (and will be referred to as the COMPASS CAD population), 27% had PAD (and will be referred to as the COMPASS PAD population), and 18% had both CAD and PAD. Of the patients with CAD, 69% had prior MI, 60% had prior percutaneous transluminal coronary angioplasty (PTCA)/atherectomy/ percutaneous coronary intervention (PCI), and 26% had history of coronary artery bypass grafting (CABG) prior to study. Of the patients with PAD, 49% had intermittent claudication, 27% had peripheral artery bypass surgery or peripheral percutaneous transluminal angioplasty, 26% had asymptomatic carotid artery stenosis > 50%, and 4% had limb or foot amputation for arterial vascular disease.

The mean duration of follow-up was 23 months. Relative to placebo, rivaroxaban reduced the rate of the primary composite outcome of stroke, myocardial infarction or cardiovascular death: HR 0.76 (95% CI: 0.66, 0.86; p=0.00004). In the COMPASS CAD population, the benefit was observed early with a constant treatment effect over the entire treatment period (see Table 26and Figure 10).

A benefit-risk analysis of the data from COMPASS was performed by comparing the number of CV events (CV deaths, myocardial infarctions and non-hemorrhagic strokes) prevented to the number of fatal or life-threatening bleeding events (fatal bleeds + symptomatic non-fatal bleeds into a critical organ) in the rivaroxaban group versus the placebo group. Compared to placebo, during 10,000 patient-years of treatment, rivaroxaban would be expected to result in 70 fewer CV events and 12 additional life-threatening bleeds, indicating a favorable balance of benefits and risks.

The results in the COMPASS CAD population were consistent across major subgroups (see Figure 9).

Figure 9: Risk of Primary Efficacy Outcome by Baseline Characteristics in the COMPASS CAD Population (Intent-to-Treat Population) [All patients received aspirin 100 mg once daily as background therapy.]

Table 26: Efficacy results from COMPASS CAD Population [intention to treat analysis set, primary analyses.]
Event | Rivaroxaban [Treatment schedule: Rivaroxaban 2.5 mg twice daily vs placebo. All patients received aspirin 100 mg once daily as background therapy.] N=8313 |  | Placebo N=8261 |  | Hazard Ratio (95% CI) [Rivaroxaban vs. placebo.]
Event | n (%) | Event Rate (%/year) | n (%) | Event Rate (%/year) | Hazard Ratio (95% CI) [Rivaroxaban vs. placebo.]
Stroke, MI or CV death | 347 (4.2) | 2.2 | 460 (5.6) | 2.9 | 0.74 (0.65, 0.86)
- Stroke | 74 (0.9) | 0.5 | 130 (1.6) | 0.8 | 0.56 (0.42, 0.75)
- MI | 169 (2.0) | 1.1 | 195 (2.4) | 1.2 | 0.86 (0.70, 1.05)
- CV death | 139 (1.7) | 0.9 | 184 (2.2) | 1.1 | 0.75 (0.60, 0.93)
Coronary heart disease death, MI, ischemic stroke, acute limb ischemia | 299 (3.6) | 1.9 | 411 (5.0) | 2.6 | 0.72 (0.62, 0.83)
- Coronary heart disease death [Coronary heart disease death: death due to acute MI, sudden cardiac death, or CV procedure.] | 80 (1.0) | 0.5 | 107 (1.3) | 0.7 | 0.74 (0.55, 0.99)
- Ischemic stroke | 56 (0.7) | 0.3 | 114 (1.4) | 0.7 | 0.49 (0.35, 0.67)
- Acute limb ischemia [Acute limb ischemia is defined as limb-threatening ischemia leading to an acute vascular intervention (i.e., pharmacologic, peripheral arterial surgery/reconstruction, peripheral angioplasty/stent, or amputation).] | 13 (0.2) | 0.1 | 27 (0.3) | 0.2 | 0.48 (0.25, 0.93)
CV death [CV death includes CHD death, or death due to other CV causes or unknown death.] , MI, ischemic stroke, acute limb ischemia | 349 (4.2) | 2.2 | 470 (5.7) | 3.0 | 0.73 (0.64, 0.84)
All-cause mortality | 262 (3.2) | 1.6 | 339 (4.1) | 2.1 | 0.77 (0.65, 0.90)
CHD: coronary heart disease, CI: confidence interval; CV: cardiovascular; MI: myocardial infarction

Figure 10: Time to First Occurrence of Primary Efficacy Outcome (Stroke, Myocardial Infarction, Cardiovascular Death) in the COMPASS CAD Population [All patients received aspirin 100 mg once daily as background therapy.]

CI: confidence interval

14.7 Reduction of Risk of Major Thrombotic Vascular Events in Patients with PAD, Including Patients after Lower Extremity Revascularization due to Symptomatic PAD

The efficacy and safety of rivaroxaban 2.5 mg orally twice daily versus placebo on a background of aspirin 100 mg once daily in patients with PAD were evaluated in the COMPASS study (n=4996) and will be referred to as the COMPASS PAD population [see Clinical Studies (14.6)] .

The efficacy and safety of rivaroxaban were also evaluated for the reduction in the risk of the composite endpoint of myocardial infarction, ischemic stroke, cardiovascular death, acute limb ischemia (ALI), and major amputation of a vascular etiology in patients undergoing a lower extremity infrainguinal revascularization procedure due to symptomatic peripheral artery disease (PAD) in the double-blinded, placebo-controlled Vascular Outcomes stud Yof ASA alon Gwith rivaroxaban in Endovascular or surgical limb Revascularization for peripheral artery disease (PAD) trial (VOYAGER) [NCT02504216]. A total of 6,564 patients were equally randomized to rivaroxaban 2.5 mg orally twice daily vs placebo on a background therapy of aspirin 100 mg once daily.

Eligible patients included adults who were at least 50 years of age with documented moderate to severe symptomatic lower extremity atherosclerotic PAD who had a successful peripheral surgical procedure and/or endovascular procedure with or without clopidogrel (up to a maximum of 6 months was allowed; median duration of therapy was 31 days). Patients had either a prior history of limb revascularization with ankle brachial index ≤0.85 or no prior history of limb revascularization with ankle brachial index ≤0.80. Patients in need of dual antiplatelet for >6 months, or any additional antiplatelet other than aspirin and clopidogrel, or oral anticoagulant, as well as patients with a history of intracranial hemorrhage, stroke, or transient ischemic attack (TIA), or patients with eGFR <15 mL/min were excluded.

The mean age was 67 years and 20% of the subject population was ≥75 years. Of the included patients, 35% had surgical revascularization, 47% had endovascular revascularization with clopidogrel, and 18% endovascular revascularization without clopidogrel. The median duration of follow-up was 30.8 months.

Rivaroxaban 2.5 mg twice daily was superior to placebo in reducing the rate of the primary composite outcome of myocardial infarction, ischemic stroke, cardiovascular death, acute limb ischemia (ALI), and major amputation of a vascular etiology. The primary efficacy outcome and its components are provided in Table 27. The Kaplan-Meier plot for the primary efficacy outcome can be seen in Figure 11. The secondary efficacy outcomes were tested for superiority in a prespecified, hierarchical order and the first five of seven endpoints were significantly reduced in the rivaroxaban treatment arm (see Table 27). Compared to placebo during 10,000 patient-years of treatment, rivaroxaban would be expected to result in 181 fewer primary outcome events and 29 more TIMI major bleeding events, indicating a favorable balance of benefits and risks.

Figure 11: Time to First Occurrence of Primary Efficacy Outcome (Myocardial Infarction, Ischemic Stroke, Cardiovascular Death, Acute Limb Ischemia, Major Amputation due to Vascular Origins) in VOYAGER [All patients received aspirin 100 mg once daily as background therapy.]

Figure 12 shows the risk of primary efficacy outcome across major subgroups. Subgroup analyses must be interpreted cautiously, as differences can reflect the play of chance among a large number of analyses. The primary efficacy endpoint generally shows homogeneous results across subgroups.

Figure 12: Risk of Primary Efficacy Outcome by Baseline Characteristics in VOYAGER (Intent-to-Treat Population) [All patients received aspirin 100 mg once daily as background therapy.]

Table 27 provides the efficacy event rates for the prespecified endpoints in VOYAGER and similar endpoints in the COMPASS PAD population.

Table 27: Efficacy Results in VOYAGER (Intent-to-Treat Population) and COMPASS PAD
 | VOYAGER |  |  | COMPASS PAD
 | Rivaroxaban N=3286 | Placebo N=3278 | Hazard Ratio (95% CI) [Rivaroxaban vs. placebo.] p-value [Two-sided p-values] | Rivaroxaban N=2492 | Placebo N=2504 | Hazard Ratio (95% CI)
Outcome Components | Event Rate (%/year) |  | Hazard Ratio (95% CI) [Rivaroxaban vs. placebo.] p-value [Two-sided p-values] | Event Rate (%/year) |  | Hazard Ratio (95% CI)
5-Component Outcome (Major thrombotic vascular events) [Major thrombotic vascular event is the composite of MI, ischemic stroke, CV death, ALI, and major amputation of a vascular etiology.] | 6.8 | 8.0 | 0.85 (0.76, 0.96) p=0.0085 | 3.4 | 4.8 | 0.71 (0.57, 0.87)
MI | 1.7 | 1.9 | 0.88 (0.70, 1.12) | 1.1 | 1.5 | 0.76 (0.53, 1.09)
Ischemic Stroke [Ischemic stroke for VOYAGER included stroke of uncertain/unknown etiology whereas COMPASS only included ischemic stroke.] | 0.9 | 1.0 | 0.87 (0.63, 1.19) | 0.5 | 0.9 | 0.55 (0.33, 0.93)
CV death [CV death includes Coronary Heart Disease death, or death due to other CV causes or sudden cardiac arrest and unknown death.] | 2.5 | 2.2 | 1.14 (0.93, 1.40) | 1.4 | 1.7 | 0.82 (0.59, 1.14)
ALI | 2.0 | 3.0 | 0.67 (0.55, 0.82) | 0.4 | 0.8 | 0.56 (0.32, 0.99)
Major amputation of a vascular etiology [Adjudicated events in VOYAGER and investigator reported events in COMPASS] | 1.3 | 1.5 | 0.89 (0.68, 1.16) | 0.2 | 0.6 | 0.40 (0.20, 0.79)
VOYAGER Secondary Efficacy Outcomes [Secondary outcomes for VOYAGER were tested sequentially.]
MI, ischemic stroke, CHD death, [CHD death includes death due to sudden cardiac death, MI, or coronary revascularization procedure] ALI, and major amputation due to vascular etiology | 5.8 | 7.3 | 0.80 (0.71, 0.91) p=0.0008 | 2.8 | 4.2 | 0.66 (0.53, 0.83)
Unplanned index limb revascularization for recurrent limb ischemia [Unplanned index limb revascularization for recurrent limb ischemia was not captured in COMPASS study.] | 8.4 | 9.5 | 0.88 (0.79, 0.99) p=0.028 | N/A | N/A | N/A
Hospitalization for a coronary or peripheral cause of a thrombotic nature | 3.5 | 4.8 | 0.72 (0.62, 0.85) p<0.0001 | 1.7 | 2.9 | 0.58 (0.44, 0.77)
MI, ischemic stroke, all-cause mortality, ALI, and major amputation due to vascular etiology | 8.2 | 9.3 | 0.89 (0.79, 0.99) p=0.029 | 4.8 | 6.0 | 0.80 (0.67, 0.96)
MI, all-cause stroke, CV death, ALI, and major amputation due to vascular etiology | 6.9 | 8.1 | 0.86 (0.76, 0.96) p=0.010 | 3.4 | 4.9 | 0.70 (0.57, 0.86)
All-cause mortality | 4.0 | 3.7 | 1.08 (0.92, 1.27) | 2.8 | 3.1 | 0.91 (0.72, 1.16)
VTE events [Investigator reported in VOYAGER and adjudicated events in COMPASS] | 0.3 | 0.5 | 0.61 (0.37, 1.00) | 0.2 | 0.3 | 0.67 (0.30, 1.49)
Efficacy endpoints in COMPASS PAD were analysed according to the pre-specified endpoints in VOYAGER when applicable.
ALI=acute limb ischemia, CHD=coronary heart disease; CI=confidence interval, CV=cardiovascular; MI=myocardial infarction, VTE=venous thromboembolism.

16 HOW SUPPLIED/STORAGE AND HANDLING

Rivaroxaban Tablets, USP are available in the strengths and packages listed below:

2.5 mg tablets are round, light yellow, film-coated and debossed on one side with "◻" and "2.5" on the other side. The tablets are supplied in the packages listed:
NDC 51672-4228-4 Bottle containing 60 tablets
NDC 51672-4228-9 Bottle containing 180 tablets
NDC 51672-4228-1 Blister package containing 100 tablets (10 blister cards containing 10 tablets each)

STORAGE AND HANDLING

Store at 20° to 25°C (68° to 77°F)[see USP Controlled Room Temperature].

Keep out of the reach of children.

17 PATIENT COUNSELING INFORMATION

For the tablets, advise the patient and/or caregiver to read the FDA-approved patient labeling (Medication Guide).

Instructions for Patient Use

- Advise patients to take rivaroxaban tablets only as directed.
- Remind patients to not discontinue rivaroxaban tablets without first talking to their healthcare professional.

Adults

- Advise patients who cannot swallow the tablet whole to crush rivaroxaban tablets and combine with a small amount of applesauce followed by food [see Dosage and Administration (2.6)] .
- For patients requiring an NG tube or gastric feeding tube, instruct the patient or caregiver to crush the rivaroxaban tablet and mix it with a small amount of water before administering via the tube [see Dosage and Administration (2.6)] .
- If a dose is missed, advise the patient according to the instructions in the Full Prescribing Information based on their dosing schedule [see Dosage and Administration (2.5)] .

Bleeding Risks

- Advise patients to report any unusual bleeding or bruising to their physician. Inform patients that it might take them longer than usual to stop bleeding, and that they may bruise and/or bleed more easily when they are treated with rivaroxaban tablets [see Warnings and Precautions (5.2)] .
- If patients have had neuraxial anesthesia or spinal puncture, and particularly, if they are taking concomitant NSAIDs or platelet inhibitors, advise patients to watch for signs and symptoms of spinal or epidural hematoma, such as back pain, tingling, numbness (especially in the lower limbs), muscle weakness, and stool or urine incontinence. If any of these symptoms occur, advise the patient to contact his or her physician immediately [see Boxed Warning] .

Invasive or Surgical Procedures

Instruct patients to inform their healthcare professional that they are taking rivaroxaban before any invasive procedure (including dental procedures) is scheduled.

Concomitant Medication and Herbals

Advise patients to inform their physicians and dentists if they are taking, or plan to take, any prescription or over-the-counter drugs or herbals, so their healthcare professionals can evaluate potential interactions [see Drug Interactions (7)] .

Pregnancy and Pregnancy-Related Hemorrhage

- Advise patients to inform their physician immediately if they become pregnant or intend to become pregnant during treatment with rivaroxaban tablets [see Use in Specific Populations (8.1)] .
- Advise pregnant women receiving rivaroxaban tablets to immediately report to their physician any bleeding or symptoms of blood loss [see Warnings and Precautions (5.7)] .

Lactation

Advise patients to discuss with their physician the benefits and risks of rivaroxaban tablets for the mother and for the child if they are nursing or intend to nurse during anticoagulant treatment [see Use in Specific Populations (8.2)] .

Females and Males of Reproductive Potential

Advise patients who can become pregnant to discuss pregnancy planning with their physician [see Use in Specific Populations (8.3)] .

Active Ingredient Made in Israel

Mfd. by: Taro Pharmaceutical Industries Ltd.

Haifa Bay, Israel 2624761

Dist. by: Sun Pharmaceutical Industries, Inc.

Cranbury, NJ 08512

Revised: June2025

Dispense with Medication Guide available at: https://www.sunpharma.com/usa/products

PRINCIPAL DISPLAY PANEL - 2.5 mg Tablet Bottle Label

NDC 51672-4228-4
60 Tablets

Rivaroxaban Tablets, USP
2.5 mg

Dispense with the accompanying Medication Guide

Rx only